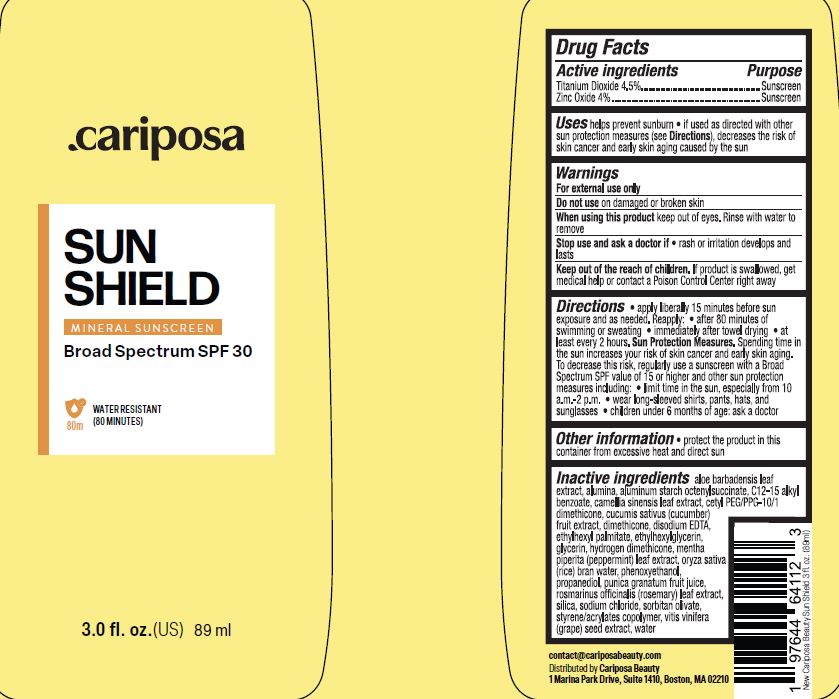 DRUG LABEL: SPF 30 Mineral Sunscreen

NDC: 84267-001 | Form: CREAM
Manufacturer: Talent Brands Company LLC
Category: otc | Type: HUMAN OTC DRUG LABEL
Date: 20240417

ACTIVE INGREDIENTS: TITANIUM DIOXIDE 4.5 g/100 mL; ZINC OXIDE 4 g/100 mL
INACTIVE INGREDIENTS: ALOE; ALUMINUM OXIDE; ALUMINUM STARCH OCTENYLSUCCINATE; ALKYL (C12-15) BENZOATE; CAMELLIA SINENSIS FLOWER; CETYL PEG/PPG-10/1 DIMETHICONE (HLB 2); CUCUMBER FRUIT OIL; DIMETHICONE; EDETATE DISODIUM; ETHYLHEXYL PALMITATE; ETHYLHEXYLGLYCERIN; GLYCERIN; HYDROGEN DIMETHICONE (13 CST); MENTHA PIPERITA; RICE BRAN, DEFATTED; PHENOXYETHANOL; PROPANEDIOL; POMEGRANATE JUICE; SALVIA ROSMARINUS FLOWER; SILICON DIOXIDE; SODIUM CHLORIDE; SORBITAN OLIVATE; STYRENE/ACRYLAMIDE COPOLYMER (500000 MW); WINE GRAPE JUICE; WATER

SPF 30 Mineral Sunscreen Cream

Active ingredients Purpose

Titanium Dioxide 4.5% Sunscreen

Zinc Oxide 4% Sunscreen

Uses

•helps prevent sunburn• If used as directed with other sun protection measures (see Oirections),decreases the risk of skin cancer and early skin aging caused by the sun.

Do not use on

• damaged or broken skin.

When using this product

•keep out of eyes. Rinse with waterto remove.

Stop use and ask a doctor if

• rash or initation develops and lasts

Directions:

• apply liberally 15 minutes before sun exposure and as needed. Reapply:

- after 80 minutes of sweeming or sweating
- immidiately after towel drying
- at least every 2 hours

Sun Protection Measures. Spending time in the sun increase your risk of skin cancer and early skin aging. To decrease this risk. regularly usea sunscreen wrtha Broad Spectrum SPF value of15 or higher and other suncrin protection measures including:
• limrt time in the sun, especial from 10a.m. -2 p.rn.•wear long-sleeve shorts , pants, hats and sunglasses

- children under 6 months of age: ask a doctor

Other information

Protect the product in this container from excessive heat and direct sun

Inactive ingredients

ALOE
ALUMINUM OXIDE
ALUMINUM STARCH OCTENYLSUCCINATE
ALKYL (C12-15) BENZOATE
CAMELLIA SINENSIS FLOWER
CETYL PEG/PPG-10/1 DIMETHICONE
CUCUMBER FRUIT OIL
DIMETHICONE
EDETATE DISODIUM
ETHYLHEXYL PALMITATE
ETHYLHEXYLGLYCERIN
GLYCERIN
HYDROGEN DIMETHICONE
MENTHA PIPERITA
Oryza Sativa Brain Water
PHENOXYETHANOL
PROPANEDIOL
POMEGRANATE JUICE
SALVIA ROSMARINUS FLOWER
SILICON DIOXIDE
SODIUM CHLORIDE
SORBITAN OLIVATE
STYRENE/ACRYLAMIDE COPOLYMER
WINE GRAPE JUICE
WATER